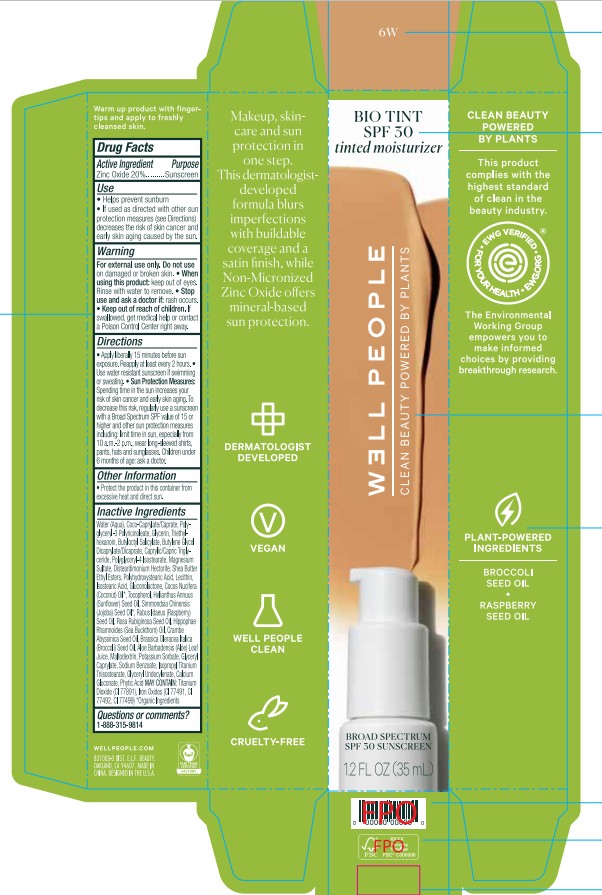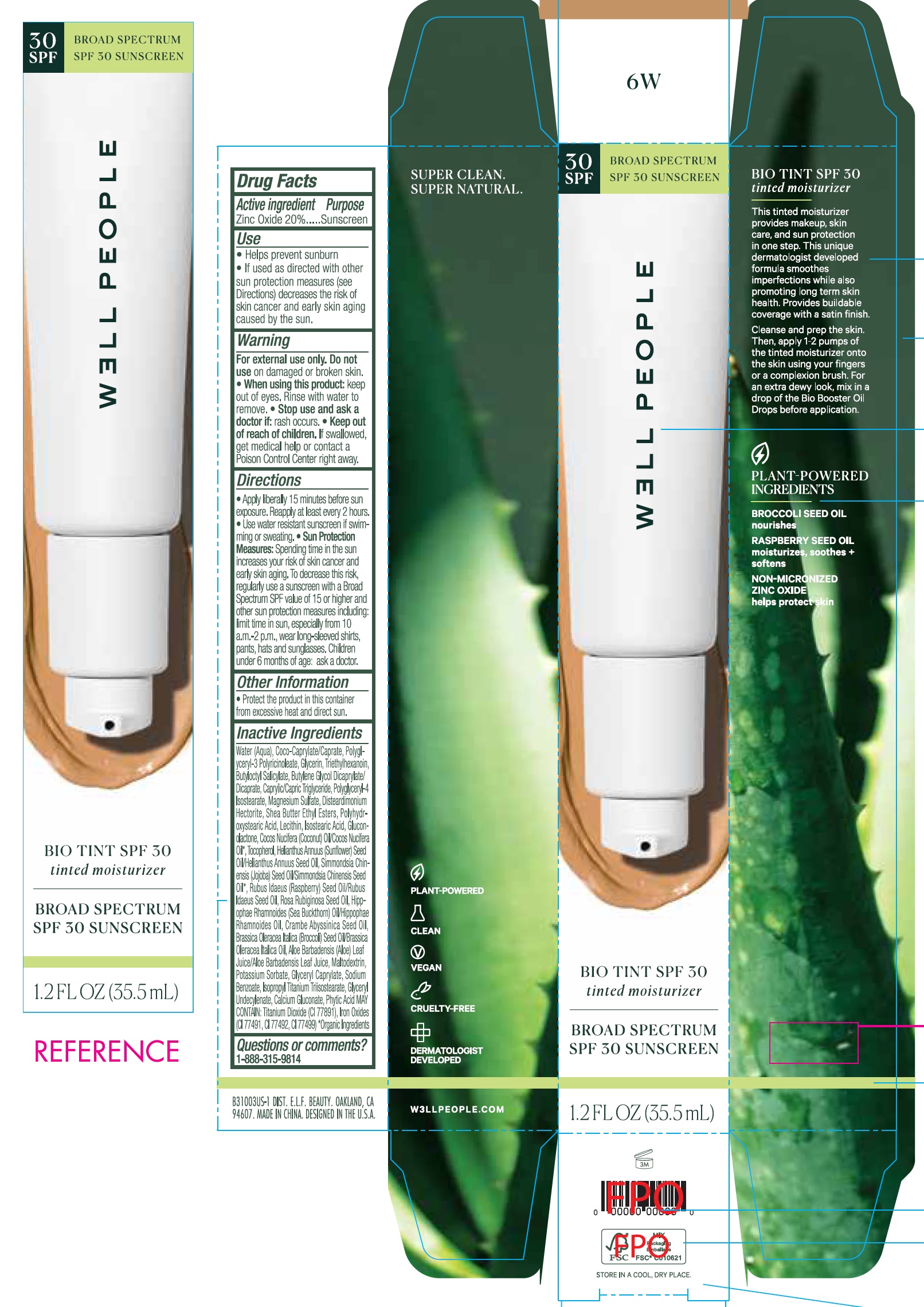 DRUG LABEL: Well People Bio Tint SPF 30 Sunscreen 6w
NDC: 76354-473 | Form: CREAM
Manufacturer: e.l.f. Cosmetics, Inc
Category: otc | Type: HUMAN OTC DRUG LABEL
Date: 20251107

ACTIVE INGREDIENTS: ZINC OXIDE 200 mg/1 mL
INACTIVE INGREDIENTS: WATER; COCOYL CAPRYLOCAPRATE; POLYGLYCERYL-3 PENTARICINOLEATE; GLYCERIN; TRIETHYLHEXANOIN; BUTYLOCTYL SALICYLATE; BUTYLENE GLYCOL; MEDIUM-CHAIN TRIGLYCERIDES; POLYGLYCERYL-4 ISOSTEARATE; MAGNESIUM SULFATE, UNSPECIFIED FORM; DISTEARDIMONIUM HECTORITE; SHEA BUTTER ETHYL ESTERS; ISOSTEARIC ACID; GLUCONOLACTONE; COCONUT OIL; TOCOPHEROL; SUNFLOWER OIL; JOJOBA OIL; RASPBERRY SEED OIL; ROSA RUBIGINOSA SEED OIL; CRAMBE HISPANICA SUBSP. ABYSSINICA SEED OIL; BROCCOLI SEED OIL; ALOE VERA LEAF; MALTODEXTRIN; POTASSIUM SORBATE; GLYCERYL CAPRYLATE; SODIUM BENZOATE; ISOPROPYL TITANIUM TRIISOSTEARATE; GLYCERYL 1-UNDECYLENATE; CALCIUM GLUCONATE; FYTIC ACID

Well People Bio Tint SPF 30 Sunscreen 6w

Active ingredient

Zinc Oxide 20%

Purpose

Sunscreen

Use

- Helps prevent sunburn
- If used as directed with other sun protection measures (see Directions) decreases the risk of skin cancer and early skin aging caused by the sun.

Warning

For external use only.

Do not use

on damaged or broken skin.

When using this product:

- keep out of eyes. Rinse with water to remove.

Stop use and ask a doctor if:

- rash occurs.

Keep out of reach of children.

If swallowed, get medical help or contact a Poison Control Center right away.

Directions

- Apply liberally 15 minutes before sun exposure. Reapply at least every 2 hours.
- Use water resistant sunscreen if swimming or sweating.
- Spending time in the sun increases your risk of skin cancer and early skin aging. To decrease this risk, regularly use a sunscreen with a Broad Spectrum SPF value of 15 or higher and other sun protection measures including:limit time in sun, especially from 10 a.m.-2 p.m., wear long-sleeved shirts, pants, hats and sunglasses. Children under 6 months of age: ask a doctor. Sun Protection Measures:

Other Information

- Protect the product in this container from excessive heat and direct sun.

Inactive Ingredients

Water (Aqua), Coco-Caprylate/Caprate, Polyglyceryl-3 Polyricinoleate, Glycerin, Triethylhexanoin, Butyloctyl Salicylate, Butylene Glycol Dicaprylate/Dicaprate, Caprylic/Capric Triglyceride, Polyglyceryl-4 Isostearate, Magnesium Sulfate, Disteardimonium Hectorite, Shea Butter Ethyl Esters, Polyhydoxystearic Acid, Lecithin, Isostearic Acid, Gluconolactone, Cocos Nucifera (Coconut) Oil/Cocos Nucifera Oil*, Tocopherol, Helianthus Annuus (Sunflower) Seed Oil/ Helianthus Annuus Seed Oil, Simmondsia Chinensis (Jojoba) Seed Oil/ Simmondsia Chinensis Seed Oil*, Rubus Idaeus (Raspberry) Seed Oil/ Rubus Idaeus Seed Oil, Rosa Rubiginosa Seed Oil, Hippophase Rhamnoides (Sea Buckthorn) Oil/Hippophae Rhamnoides Oil, Crambe Abyssinica Seed Oil, Brassica Oleracea Italica (Broccoli) Seed Oil/ Brasica Oleracea Italica Oil, Aloe Barbadensis (Aloe) Leaf Juice/Aloe Barbadensis Leaf Juice, Maltodextrin, Potassium Sorbate, Glyceryl Caprylate, Sodium Benzoate, Isopropyl Titanium Triisostearate, Glyceryl Undecylenate, Calcium Gluconate, Phytic Acid MAY CONTAIN: Titanium Dioxide (CI 77891), Iron Oxides (CI 77491, CI 77492, CI 77499) *Organic Ingredients

Questions or comments?

1-888-315-9814